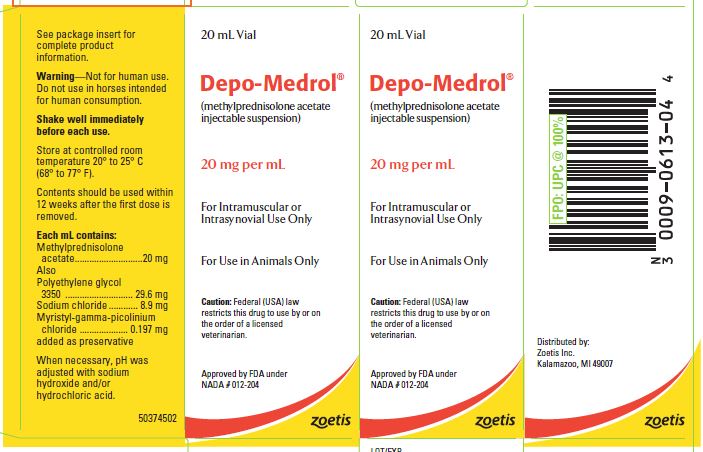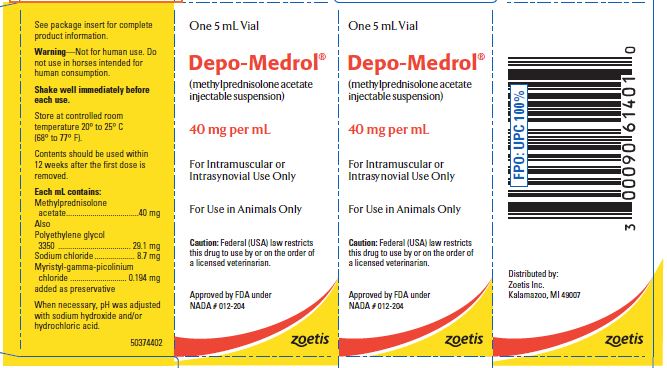 DRUG LABEL: Depo-Medrol
NDC: 54771-1613 | Form: INJECTION, SUSPENSION
Manufacturer: Zoetis Inc.
Category: animal | Type: PRESCRIPTION ANIMAL DRUG LABEL
Date: 20211208

ACTIVE INGREDIENTS: METHYLPREDNISOLONE ACETATE 20 mg/1 mL
INACTIVE INGREDIENTS: POLYETHYLENE GLYCOL 3350 29.6 mg/1 mL; SODIUM CHLORIDE

Depo-Medrol®

(methylprednisolone acetate injectable suspension)

20 mg per mL and 40 mg per mL

For Use in Animals Only

Caution

Federal (USA) law restricts this drug to use by or on the order of a licensed veterinarian.

DESCRIPTION

These preparations are recommended for intramuscular and intrasynovial injection in horses and dogs, and intramuscular injection in cats. DEPO-MEDROL is available in two concentrations, 20 mg per mL and 40 mg per mL. Each mL of these preparations contains:

 | 20 mg | 40 mg
Methylprednisolone acetate | 20 mg | 40 mg
Polyethylene glycol 3350 | 29.6 mg | 29.1 mg
Sodium chloride | 8.9 mg | 8.7 mg
Myristyl-gamma-picolinium chloride added as preservative | 0.197 mg | 0.194 mg
When necessary, pH was adjusted with sodium hydroxide and/or hydrochloric acid.
The chemical name for methylprednisolone acetate is pregna-1,4-diene-3,20-dione, 21-(acetyloxy)-11,17-dihydroxy-6-methyl-, (6α,11ß)-

CLINICAL PHARMACOLOGY

Metabolic and Hormonal Effects

Methylprednisolone, an anti-inflammatory steroid synthesized and developed in the
Research Laboratories of The Upjohn Company, is the 6-methyl derivative of
prednisolone. Exceeding prednisolone in anti-inflammatory potency and having even
less tendency than prednisolone to induce sodium and water retention,methylprednisolone
offers the advantage over older corticosteroids of affording
equally satisfactory anti-inflammatory effect with the use of lower doses and with an
enhanced split between anti-inflammatory and mineralocorticoid activities. Estimates
of the relative potencies of methylprednisolone and prednisolone range from
1.13 to 2.1, with an average of 1.5. In anti-inflammatory activity, as measured by the
granuloma pouch assay, methylprednisolone is twice as active as prednisolone. In
mineralocorticoid activity (ie, the capacity to induce retention of sodium and water in
the adrenalectomized rat) methylprednisolone is slightly less active than prednisolone.
The duration of plasma steroid levels following rapid intravenous injection in intact
dogs is appreciably longer for methylprednisolone than for prednisolone, the
respective “half-life” value for the two steroids being 80.9 ± 7.5 minutes for methylprednisolone
and 71.3 ±1.7 minutes for prednisolone.

While the effect of parenterally administered DEPO-MEDROL is prolonged, it has
the same metabolic and anti-inflammatory actions as orally administered methylprednisolone
acetate.

INDICATIONS AND USAGE

Musculoskeletal Conditions

As with other adrenal steroids, DEPO-MEDROL has
been found useful in alleviating the pain and lameness associated with acute localized
arthritic conditions and generalized arthritic conditions. It has been used successfully
to treat rheumatoid arthritis, traumatic arthritis, osteoarthritis, periostitis, tendinitis,
synovitis, tenosynovitis, bursitis, and myositis of horses; traumatic arthritis,
osteoarthritis, and generalized arthritic conditions of dogs. Remission of musculoskeletal
conditions may be permanent, or symptoms may recur, depending on the cause and
extent of structural degeneration.

Allergic Conditions

This preparation is especially beneficial in relieving pruritus
and inflammation of allergic dermatitis, acute moist dermatitis, dry eczema, urticaria,
bronchial asthma, pollen sensitivities and otitis externa in dogs; allergic dermatitis and
moist and dry eczema in cats. Onset of relief may begin within a few hours to a few
days following injection and may persist for a few days to six weeks. Symptoms may
be expected to recur if the cause of the allergic reaction is still present, in which case
retreatment may be indicated. In treating acute hypersensitivity reactions, such as
anaphylactic shock, intravenous SOLU-DELTA-CORTEF® Sterile Powder containing
prednisolone sodium succinate, as well as other appropriate treatments, should be
used.

Overwhelming Infections with Severe Toxicity

In dogs and cats moribund from
overwhelmingly severe infections for which antibacterial therapy is available (eg,
critical pneumonia, pyometritis), DEPO-MEDROL may be lifesaving, acting to inhibit
the inflammatory reaction, which itself may be lethal; preventing vascular collapse
and preserving the integrity of the blood vessels; modifying the patient’s reaction to
drugs; and preventing or reducing the exudative reaction which often complicates
certain infections. As supportive therapy, it improves the general attitude of the animal
being treated. All necessary procedures for the establishment of a bacterial diagnosis
should be carried out whenever possible before institution of therapy. Corticosteroid
therapy in the presence of infection should be administered for the shortest possible
time compatible with maintenance of an adequate response, and antibacterial therapy
should be continued for at least three days after the hormone has been withdrawn.
Combined hormone and antibacterial therapy does not obviate the need for indicated
surgical treatment.

Other Conditions

In certain conditions where it is desired to reduce inflammation,
vascularization, fibroblastic infiltration, and scar tissue, the use of DEPO-MEDROL
should be considered. Snakebite of dogs also is an indication for the use of this
suspension because of its anti-toxemic, anti-shock, and anti-inflammatory activity. It
is particularly effective in reducing swelling and preventing sloughing. Its employment
in the treatment of such conditions is recommended as a supportive measure to
standard procedures and time-honored treatments and will give comfort to the animal
and hasten complete recovery.

CONTRAINDICATIONS

Systemic therapy with methylprednisolone acetate, as with other corticoids, is
contraindicated in animals with arrested tuberculosis, peptic ulcer, and Cushing’s
syndrome. The presence of active tuberculosis, diabetes mellitus, osteoporosis, renal
insufficiency, predisposition to thrombophlebitis, hypertension, or congestive heart
failure necessitates carefully controlled use of corticosteroids. Intrasynovial,
intratendinous, or other injections of corticosteroids for local effect are contraindicated
in the presence of acute infectious conditions. Exacerbation of pain, further loss of
joint motion, with fever and malaise following injection may indicate that the condition
has become septic. Appropriate antibacterial therapy should be instituted immediately.

WARNING

Clinical and experimental data have demonstrated that corticosteroids administered
orally or parenterally to animals may induce the first stage of parturition when administered
during the last trimester of pregnancy and may precipitate premature
parturition followed by dystocia, fetal death, retained placenta and metritis.

Additionally, corticosteroids administered to dogs, rabbits, and rodents during
pregnancy have resulted in cleft palate in offspring. Corticosteroids administered to
dogs during pregnancy have also resulted in other congenital anomalies, including
deformed forelegs, phocomelia, and anasarca.

Not for human use. Do not use in horses intended for human consumption.

PRECAUTIONS

DEPO-MEDROL exerts an inhibitory influence on the mechanisms and the tissue
changes associated with inflammation. Vascular permeability is decreased, exudation
diminished, and migration of the inflammatory cells markedly
inhibited. In addition, systemic manifestations such as fever and signs of toxemia may also be suppressed.
While certain aspects of this alteration of the inflammatory reaction may be beneficial,
the suppression of inflammation may mask the signs of infection and tend to facilitate
spread of microorganisms. Hence, all patients receiving this drug should be watched
for evidence of intercurrent infection. Should infection occur, it must be brought under
control by the use of appropriate antibacterial measures, or administration of this preparation
should be discontinued. However, in infections characterized by
overwhelming toxicity, methylprednisolone acetate therapy in conjunction with
appropriate antibacterial therapy is effective in reducing mortality and morbidity.
Without conjoint use of an antibiotic to which the invader-organism is sensitive,
injudicious use of the adrenal hormones in animals with infections can be hazardous.
As with other corticoids, continued or prolonged use is discouraged.

While no sodium retention or potassium depletion has been observed at the doses
recommended, animals receiving methylprednisolone acetate, as with all corticoids,
should be under close observation for possible untoward effects. If symptoms of
hypopotassemia (hypokalemia) should occur, corticoid therapy should be discontinued
and potassium chloride administered by continuous intravenous drip.

Since this drug lacks significant mineralocorticoid activity in usual therapeutic
doses, it is not likely to afford adequate support in states of acute adrenocortical
insufficiency. For treatment of the latter, the parent adrenocortical steroids,
hydrocortisone or cortisone, should be used.

DOSAGE AND ADMINISTRATION

INTRAMUSCULAR

Following intramuscular injection of methylprednisolone acetate, a prolonged systemic effect results. The dose varies with the size of the animal patient, the severity of the condition under treatment, and the animal’s response to therapy.

Dogs and Cats

The average intramuscular dose for dogs is 20 mg. In accordance with the size of the dog and severity of the condition under treatment, the dose may range from 2 mg in miniature breeds to 40 mg in medium breeds, and even as high as 120 mg in extremely large breeds or dogs with severe involvement.
The average intramuscular dose for cats is 10 mg with a range up to 20 mg.
Injections may be made at weekly intervals or in accordance with the severity of the condition and clinical response.

Horses

The usual intramuscular dose for horses is 200 mg repeated as necessary.
For maintenance therapy in chronic conditions, initial doses should be reduced gradually until the smallest effective (ie, individualized) dose is established. MEDROL® Tablets containing methylprednisolone may also be used for maintenance in dogs and cats, administered according to the recommended dose.
When treatment is to be withdrawn after prolonged and intensive therapy, the dose should be reduced gradually.
If signs of stress are associated with the condition being treated, the dose should be increased. If a rapid hormonal effect of maximum intensity is required, as in anaphylactic shock, the intravenous administration of highly soluble SOLU-DELTA-CORTEF® Sterile Powder containing prednisolone sodium succinate is indicated.

INTRASYNOVIAL

Methylprednisolone acetate, a slightly soluble ester of methylprednisolone, is capable of producing a more prolonged local anti-inflammatory effect than equimolar doses of hydrocortisone acetate. Following intrasynovial injection, relief from pain may be experienced within 12 to 24 hours. The duration of relief varies, but averages three to four weeks, with a range of one to five or more weeks. Injections of methylprednisolone acetate have been well tolerated. Intrasynovial (intra-articular) injections may occasionally result in an increased localized inflammatory response.
Intrasynovial injection is recommended as an adjuvant to general therapeutic measures to effect suppression of inflammation in one or a few peripheral structures when (1) the disease is limited to one or a few peripheral structures; (2) the disease is widespread with one or a few peripheral structures actively inflamed; (3) systemic therapy with other corticoids or corticotropin controls all but a few of the more actively involved structures; (4) systemic therapy with cortisone, hydrocortisone, or corticotropin is contraindicated; (5) joints show early but actively progressing deformity (to enhance the effect of physiotherapy and corrective procedures); and (6) surgical or other orthopedic corrective measures are to be or have been done.
The action of DEPO-MEDROL injected intrasynovially appears to be well localized since significant metabolic effects characteristic of systemic administration of adrenal steroids have not been observed. In a few instances mild and transient improvement of structures other than those injected have been reported. No other systemic effects have been noted. However, it is possible that mild systemic effects may occur following intrasynovial administration, and this possibility is greater the larger the number of structures injected and the higher the total dose employed.

Procedure for Intrasynovial Injection

The anatomy of the area to be injected should be reviewed in order to assure that the suspension is properly placed and to determine that large blood vessels or nerves are avoided. The injection site is located where the synovial cavity is most superficial. The area is prepared for aseptic injection of the medicament by the removal of hair and cleansing of the skin with alcohol or Mercresin® tincture. A sterile 18- to 21-gauge needle for horses, 20- to 22-gauge needle for dogs, on a dry syringe is quickly inserted into the synovial space and a small amount of synovial fluid withdrawn. If there is an excess of synovia and more than 1 mL of suspension is to be injected, it is well to aspirate a volume of fluid comparable to that which is to be injected. With the needle in place, the aspirating syringe is removed and replaced by a second syringe containing the proper amount of suspension which is then injected. In some animals a transient pain is elicited immediately upon injection into the affected cavity. This pain varies from mild to severe and may last for a few minutes up to 12 hours. After injection, the structure may be moved gently a few times to aid mixing of the synovial fluid and the suspension. The site may be covered with a small sterile dressing.
Areas not suitable for injection are those that are anatomically inaccessible such as spinal joints and those like the sacroiliac joints, which are devoid of synovial space. Treatment failures are most frequently the result of failure to enter the synovial space. If failures occur when injections into the synovial spaces are certain, as determined by aspiration of fluid, repeated injections are usually futile. Local therapy does not alter the underlying disease process, and whenever possible comprehensive therapy including physiotherapy and orthopedic correction should be employed.
The single intrasynovial dose depends on the size of the part, which corresponds to the size of the animal. The interval between repeated injections depends on the duration of relief obtained.

Horses

The average initial dose for a large synovial space in horses is 120 mg with a range from 40 to 240 mg. Smaller spaces will require a correspondingly lesser dose.

Dogs

The average initial dose for a large synovial space in dogs is 20 mg. Smaller spaces will require a correspondingly lesser dose.

STORAGE AND HANDLING

Store at controlled room temperature 20° to 25° C (68° to 77° F).

Contents should be used within 12 weeks after the first dose is removed.

HOW SUPPLIED

DEPO-MEDROL, 20 mg/mL is available in 20 mL vials, and 40 mg/mL is available in 5 mL vials.

Approved by FDA under NADA # 012-204
zoetis
Distributed by:
Zoetis Inc.
Kalamazoo, MI 49007
Revised: May 2019
50334301

PRINCIPAL DISPLAY PANEL - 20 mg Vial Carton

Depo-Medrol 20 mg

PRINCIPAL DISPLAY PANEL - 40 mg Vial Carton

Depo-Medrol 40 mg